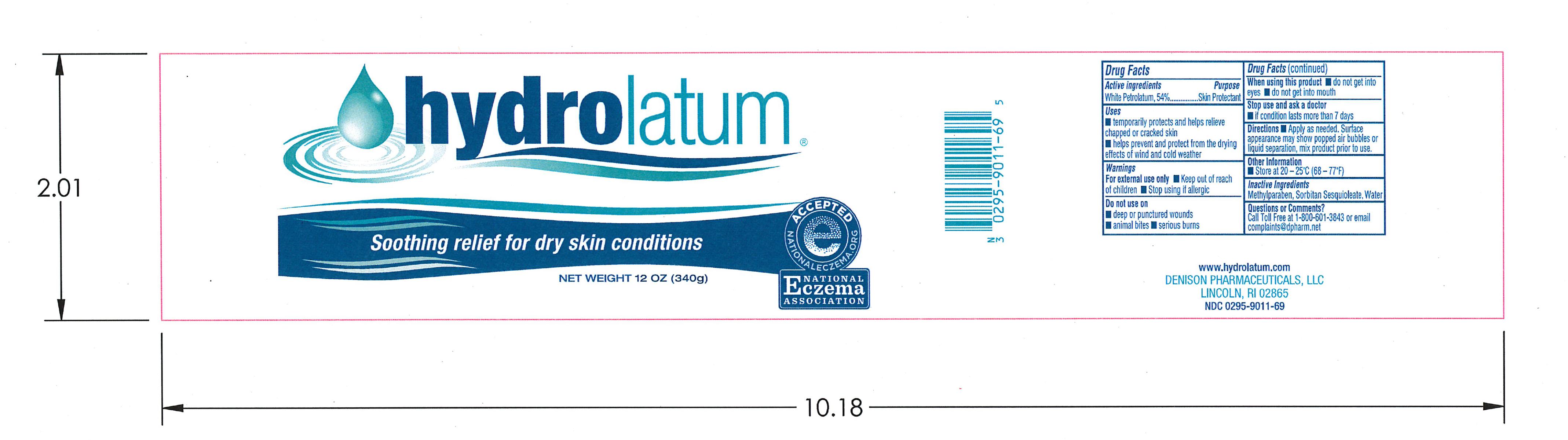 DRUG LABEL: Hydrolatum
NDC: 0295-9011 | Form: CREAM
Manufacturer: Denison Pharmaceuticals, LLC
Category: otc | Type: HUMAN OTC DRUG LABEL
Date: 20231011

ACTIVE INGREDIENTS: PETROLATUM 45 g/100 g
INACTIVE INGREDIENTS: WATER; SORBITAN SESQUIOLEATE; METHYLPARABEN

Hydrolatum

ACTIVE INGREDIENT

White Petrolatum, 54%

PURPOSE

Skin Protectant

INDICATIONS AND USAGE

- temporarily protects and helps relieve chapped or cracked skin
- helps prevent and protect from the drying effects of wind and cold weather

WARNINGS

- for external use only
- Keep out of reach of children
- Stop using if allergic

WHEN USING

- do not get into eyes
- do not get into mouth

STOP USE

- if condition lasts more than 7 days

DOSAGE AND ADMINISTRATION

- apply as needed

OTHER SAFETY INFORMATION

- Store at 20-25C (68-77F)

INACTIVE INGREDIENT

Methylparaben, Purified Water, Sorbitan Sesquioleate

TROUBLESHOOTING

Call Toll Free at 1-800-601-3843 or email complaints@dpharm.net

DO NOT USE

- deep or punctured wounds
- animal bites
- serious burns

Keep out of reach of children